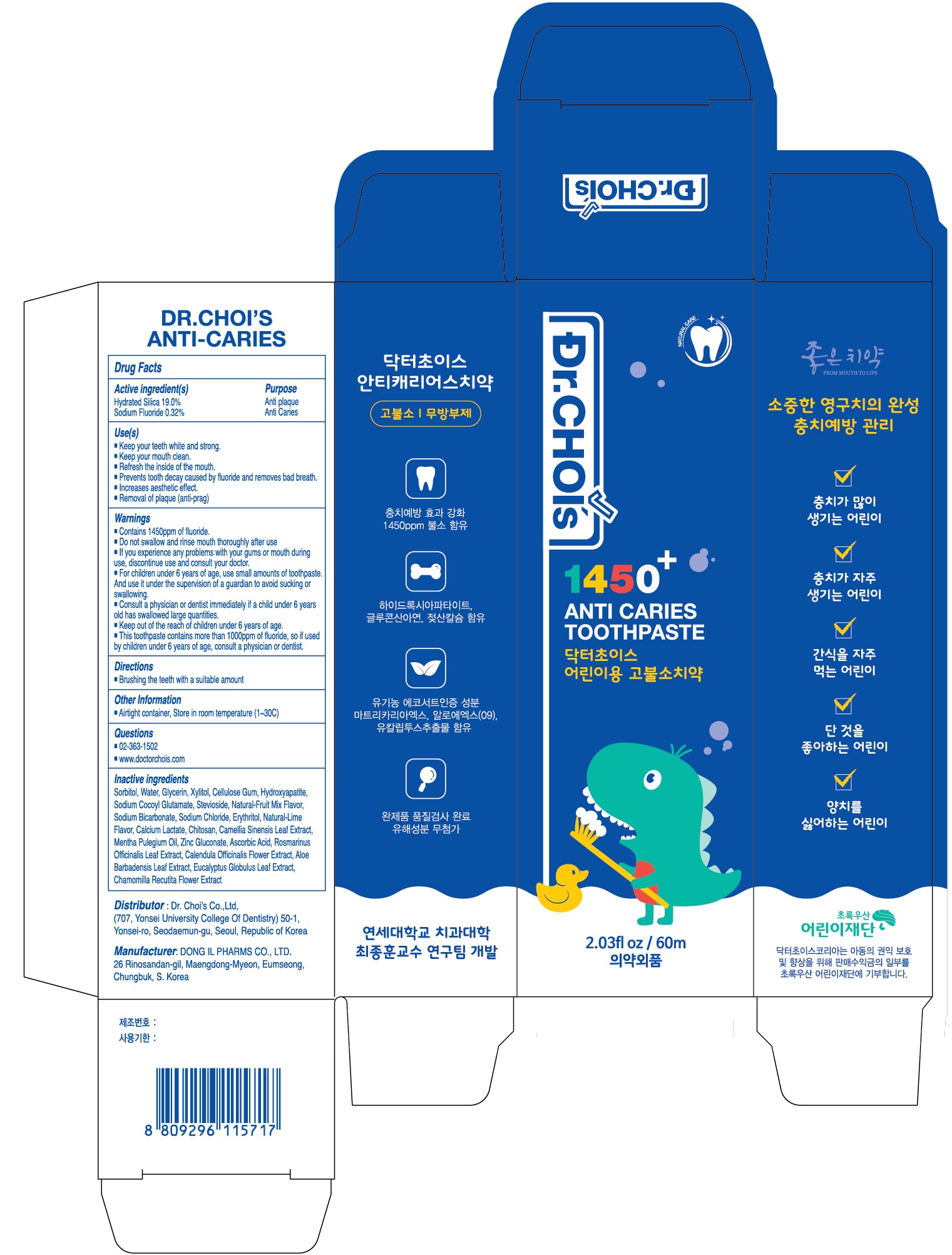 DRUG LABEL: Dr.Chois 1450 Anti Caries Toothpaste
NDC: 73666-0610 | Form: PASTE, DENTIFRICE
Manufacturer: Doctor Choi`s Korea Co., LTD.
Category: otc | Type: HUMAN OTC DRUG LABEL
Date: 20240416

ACTIVE INGREDIENTS: SILICON DIOXIDE 19.0 g/100 mL; Sodium Fluoride 0.32 g/100 mL
INACTIVE INGREDIENTS: Sorbitol; Water; Glycerin

ACTIVE INGREDIENTS

Hydrated Silica 19.0%
Sodium Fluoride 0.32%

PURPOSE

Anti plaque
Anti Caries

Uses

■ Keep your teeth white and strong.
■ Keep your mouth clean.
■ Refresh the inside of the mouth.
■ Prevents tooth decay caused by fluoride and removes bad breath.
■ Increases aesthetic effect.
■ Removal of plaque (anti-prag)

WARNINGS

■ Contains 1450ppm of fluoride.
■ Do not swallow and rinse mouth thoroughly after use
■ If you experience any problems with your gums or mouth during use,
discontinue use and consult your doctor.
■ For children under 6 years of age, use small amounts of toothpaste. And use it
under the supervision of a guardian to avoid sucking or swallowing.
■ Consult a physician or dentist immediately if a child under 6 years old has
swallowed large quantities.
■ Keep out of the reach of children under 6 years of age.
■ This toothpaste contains more than 1000ppm of fluoride, so if used by children under 6 years of age, consult a physician or dentist.

KEEP OUT OF REACH OF CHILDREN

■ Keep out of the reach of children under 6 years of age.
■ This toothpaste contains more than 1000ppm of fluoride, so if used by children under 6 years of age, consult a physician or dentist.

Directions

■ Brushing the teeth with a suitable amount

Other Information

■ Airtight container, Store in room temperature (1~30C)

Questions

■ 02-363-1502
■ www.doctorchois.com

INACTIVE INGREDIENTS

Sorbitol, Water, Glycerin, Xylitol, Cellulose Gum, Hydroxyapatite, Sodium Cocoyl Glutamate, Stevioside, Natural-Fruit Mix Flavor, Sodium Bicarbonate, Sodium Chloride, Erythritol, Natural-Lime Flavor, Calcium Lactate, Chitosan, Camellia Sinensis Leaf Extract, Mentha Pulegium Oil, Zinc Gluconate, Ascorbic Acid, Rosmarinus Officinalis Leaf Extract, Calendula Officinalis Flower Extract, Aloe Barbadensis Leaf Extract, Eucalyptus Globulus Leaf Extract, Chamomilla Recutita Flower Extract